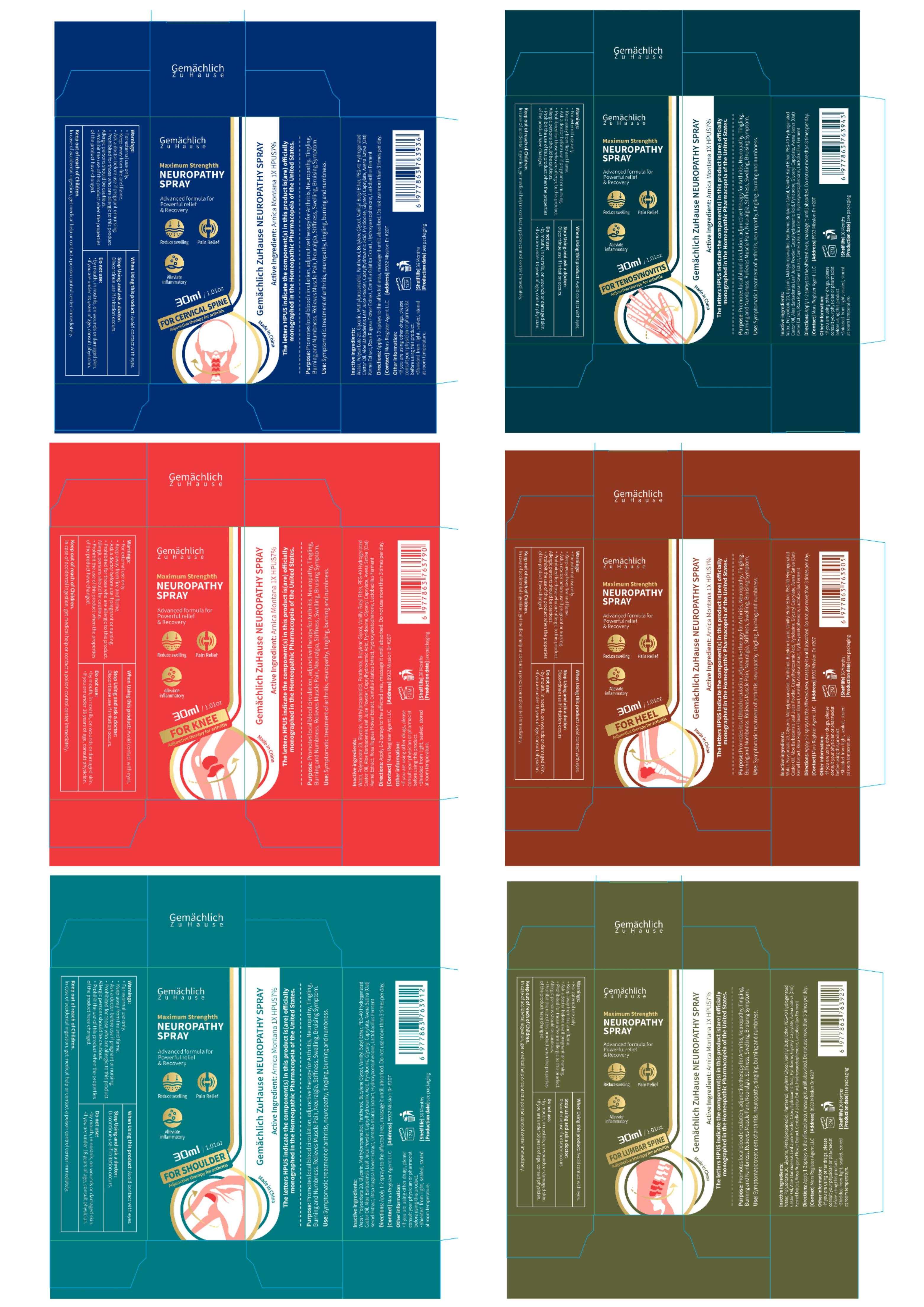 DRUG LABEL: Gemachlich ZuHause NEUROPATHY Spray.
NDC: 76986-014 | Form: SPRAY
Manufacturer: Guangdong Quadrant Ecological Technology Co., Ltd.
Category: otc | Type: HUMAN OTC DRUG LABEL
Date: 20251030

ACTIVE INGREDIENTS: ARNICA MONTANA 7 g/100 mL
INACTIVE INGREDIENTS: BUTYLENE GLYCOL; ALOE BARBADENSIS LEAF JUICE; ROSA RUGOSA FLOWER; PANTHENOL; PEG-40 HYDROGENATED CASTOR OIL; AVENA SATIVA (OAT) KERNEL OIL; PEG-80 SORBITAN LAURATE; GLYCERIN; WATER; PYRIDOXINE; LIMOSILACTOBACILLUS FERMENTUM; METHYLPROPANEDIOL; HYDROXYACETOPHENONE; CENTELLA ASIATICA; GLYCERYL CAPRYLATE; VANILLYL BUTYL ETHER; CAPRYLHYDROXAMIC ACID

76986-014

Active Ingredient

ARNICA MONTANA 7%

Purpose

Promotes local blood circulation, adjunctive therapy for Arthritis、Neuropathy,Tingling, Burning and Numbness. Relieves Muscle Pain, Neuralgia, Stiffness,Swelling,Bruising Symptom.

Use

Symptomatic treatment of arthritis,neuropathy,tingling, burning and numbness .

Warnings

· For external use only.
· Keep away from fire and flame.
· Ask a doctor before use if pregnant or nursing.
· Prohibited for those who are allergic to this product. Allergic persons should be cautious.
· Prohibit the use of this product when the properties of the product have changed.

Do not use

·by mouth,in nostrils,on wounds or damaged skin.
·if you are under 18 years of age,consult physician.

When Using

Avoid contact with eyes.

Stop Use

Discontinue use if irritation occurs.

Ask Doctor

Discontinue use if irritation occurs.

Keep Out Of Reach Of Children

In case of accidental ingestion, get medical help or contact a poison control center immediately.

Directions

Apply 1-2 sprays to the affected area ,massage it untill absorbed.Do not use more than 3 times per day.

Other information

·If you are using other drugs, please consult your physician or pharmacist before using this product.
·Shielded from light, sealed, stored at room temperature.

Inactive ingredients

Water, Polysorbate 20, Glycerin, Methylpropanediol, Panthenol, Butylene Glycol, Vanillyl Butyl Ether, PEG-40 Hydrogenated Castor Oil, Aloe Barbadensis Leaf Juice Powder, Caprylhydroxamic Acid, Pyridoxine, Glyceryl Caprylate, Avena Sativa (Oat) Kernel Extract, Rosa Rugosa Flower Extract, Centella Asiatica Extract, Hydroxyacetophenone, Lactobacillus Ferment